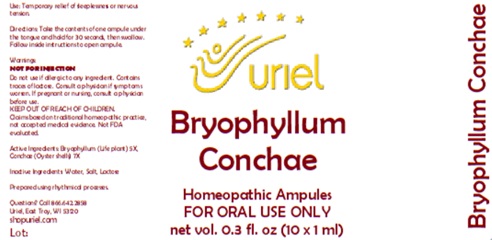 DRUG LABEL: Bryophyllum Conchae
NDC: 48951-2150 | Form: LIQUID
Manufacturer: Uriel Pharmacy Inc.
Category: homeopathic | Type: HUMAN OTC DRUG LABEL
Date: 20260203

ACTIVE INGREDIENTS: KALANCHOE DAIGREMONTIANA LEAF 5 [hp_X]/1 mL; OSTREA EDULIS SHELL 7 [hp_X]/1 mL
INACTIVE INGREDIENTS: WATER; SODIUM CHLORIDE; LACTOSE

Bryophyllum Conchae

PURPOSE

Use: Temporary relief of sleeplessness.

INDICATIONS AND USAGE

FOR ORAL USE ONLY

DOSAGE AND ADMINISTRATION

Directions: Take the contents of one ampule under the tongue and hold for 30 seconds, then swallow. Follow inside instructions to open ampule.

Warnings:
NOT FOR INJECTION
Do not use if allergic to any ingredient. Contains traces of lactose. Consult a physician if symptoms worsen. If pregnant or nursing, consult a physician before use.
Claims based on traditional homeopathic practice, not accepted medical evidence. Not FDA evaluated.

KEEP OUT OF REACH OF CHILDREN.

ACTIVE INGREDIENT

Active Ingredients: Bryophyllum (Life plant) 5X, Conchae (Oyster shells) 7X

Inactive Ingredients: Water, Salt, Lactose

Prepared using rhythmical processes.

QUESTIONS

Questions? Call 866.642.2858 Uriel, East Troy, WI 53120 shopuriel.com Lot: